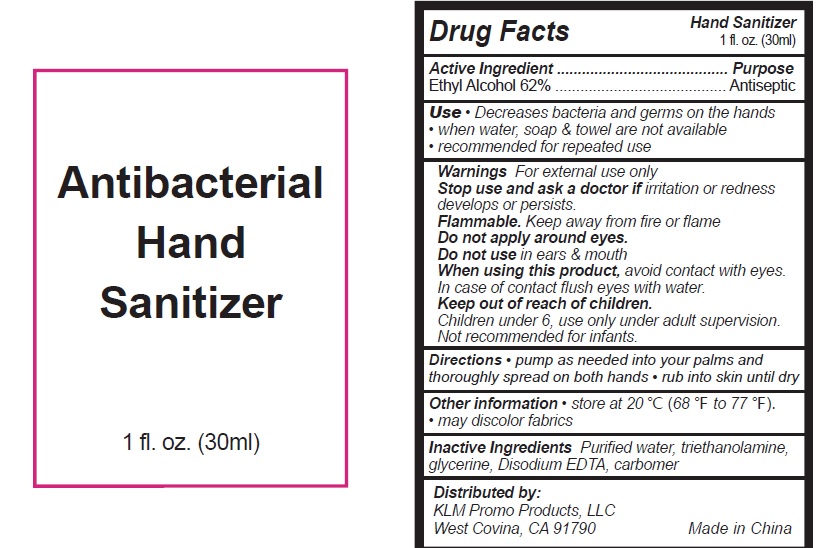 DRUG LABEL: Antibacterial Hand Sanitizer
NDC: 71734-300 | Form: GEL
Manufacturer: JIANGMEN SHUIZIRUN SANITARY ARTICLES CO., LTD.
Category: otc | Type: HUMAN OTC DRUG LABEL
Date: 20200428

ACTIVE INGREDIENTS: alcohol 62 mL/100 mL
INACTIVE INGREDIENTS: WATER; PROPYLENE GLYCOL; EDETATE DISODIUM; GLYCERIN; TROLAMINE

Drug facts

Active ingredient(s) Purpose

Ethyl Alcohol 62% ............... Antiseptic

PURPOSE

- Decrease bacteria and germs on the hans
- when water, soap and towel are not available
- recommended for reapeated use

KEEP OUT OF REACH OF CHILDREN

Children under 6, use only under adult supervision. Not recommended for infants.

INDICATIONS AND USAGE

keep out of eyes

when water, soap and towel are not available

WARNINGS

For external use only.
Flammable. Keep away from fire or flame.

Do not apply aroun eyes.

Do not use in ears and mouth

When using this produt, avoid contact with eyes. In case of contact flush eyes with water.

DOSAGE AND ADMINISTRATION

Pump as needed into your palms and thoroughly spread on both hands, and rub the skin until dry.

Other information:

- store at 20℃(68℉-77℉)
- may disolor fabrics

INACTIVE INGREDIENT

Purified Water, Triethanolamine, Glycerin, Disodium EDTA, carbomer